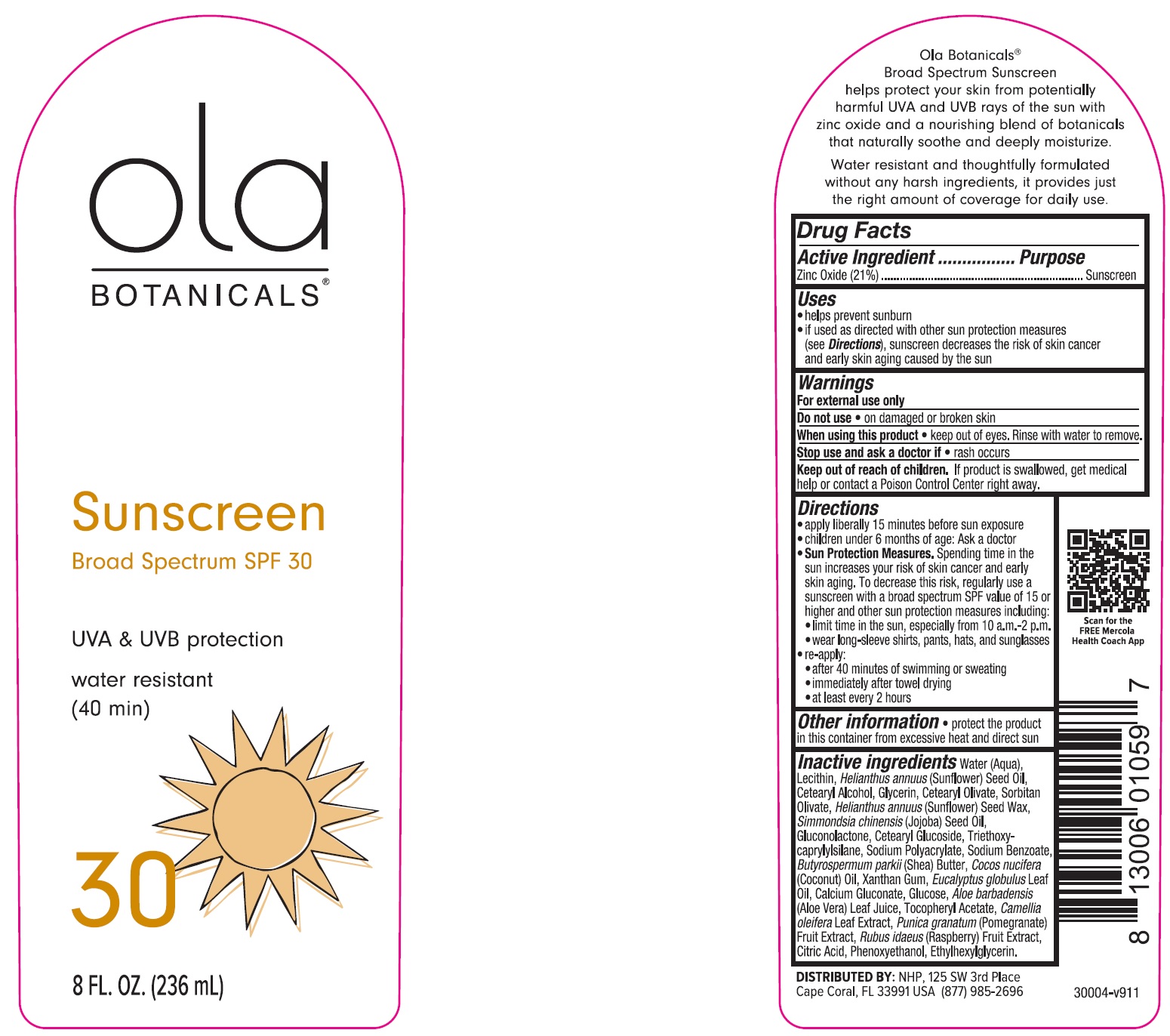 DRUG LABEL: Ola Botanicals Sunscreen SPF 30
NDC: 71239-845 | Form: LOTION
Manufacturer: Natural Health Partners, LLC
Category: otc | Type: HUMAN OTC DRUG LABEL
Date: 20250602

ACTIVE INGREDIENTS: ZINC OXIDE 210 mg/1 mL
INACTIVE INGREDIENTS: WATER; SUNFLOWER OIL; CETEARYL ALCOHOL; GLYCERIN; CETEARYL OLIVATE; HELIANTHUS ANNUUS SEED WAX; JOJOBA OIL; GLUCONOLACTONE; CETEARYL GLUCOSIDE; TRIETHOXYCAPRYLYLSILANE; SODIUM BENZOATE; SHEA BUTTER; COCONUT OIL; XANTHAN GUM; EUCALYPTUS OIL; CALCIUM GLUCONATE; ANHYDROUS DEXTROSE; .ALPHA.-TOCOPHEROL ACETATE; CAMELLIA OLEIFERA LEAF; POMEGRANATE; RASPBERRY; CITRIC ACID MONOHYDRATE; PHENOXYETHANOL; ETHYLHEXYLGLYCERIN

Ola Botanicals Sunscreen SPF 30

Active Ingredient

Zinc Oxide (21%)

Purpose

Sunscreen

Uses

- helps prevent sunburn.
- if used as directed with other sun protection measures (see Directions), sunscreen decreases the risk of skin cancer and early skin aging caused by the sun

Warnings

For external use only

Do not use

- on damaged or broken skin

When using this product

- keep out of eyes. Rinse with water to remove.

Stop use and ask a doctor if

- rash occurs

Keep out of reach of children.

If product is swallowed, get medical help or contact a Poison Control Center right away.

Directions

- apply liberally 15 minutes before sun exposure
- children under 6 months of age: Ask a doctor
- Sun Protection Measures.Spending time in the sun increases your risk of skin cancer and early skin aging. To decrease this risk, regularly use a sunscreen with broad spectrum SPF value of 15 or higher and other sun protection measures including:
- limit time in the sun, especially from 10 a.m. - 2 p.m.
- wear long-sleeve shirts, pants, hats, and sunglasses
- re-apply:
- after 40 minutes of swimming or sweating
- immediately after towel drying
- at least every 2 hours

Other information

- protect the product in this container from excessive heat and direct sun

Inactive ingredients

Water (Aqua), Lecithin, Helianthus annuus (Sunflower) Seed OIl, Cetearyl Alcohol, Glycerin, Cetearyl Olivate, Helianthus annuus (Sunflower) Seed Wax, Simmondsia chinensis (Jojoba) Seed Oil, Gluconolactone, Cetearyl Glucoside, Triethoxy-caprylylsilane, Sodium Polyacrylate, Sodium Benzoate, Butyrospermum parkii (Shea) Butter, Cocos nucifera (Coconut) Oil, Xanthan Gum, Eucalyptus globulus Leaf Oil, Calcium Gluconate, Glucose, Aloe barbadensis (Aloe Vera) Leaf Juice, Tocopheryl Acetate, Camellia oleifera Leaf Extract, Punica granatum (Pomegranate) Fruit Extract, Rubus idaeus (Raspberry) Fruit Extract, Citric Acid, Phenoxyethanol, Ethylhexylglycerin.